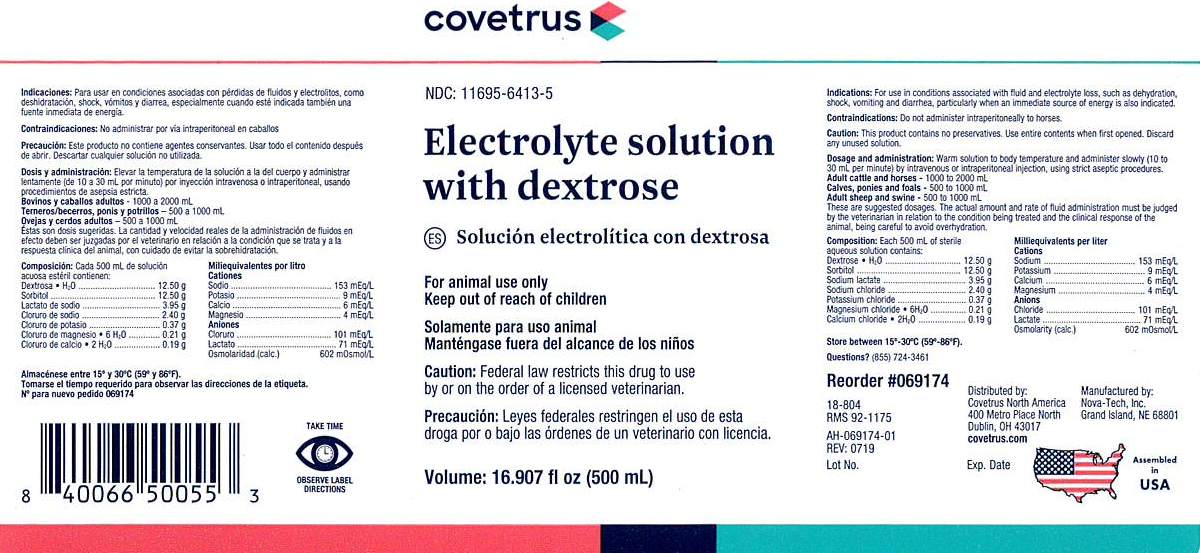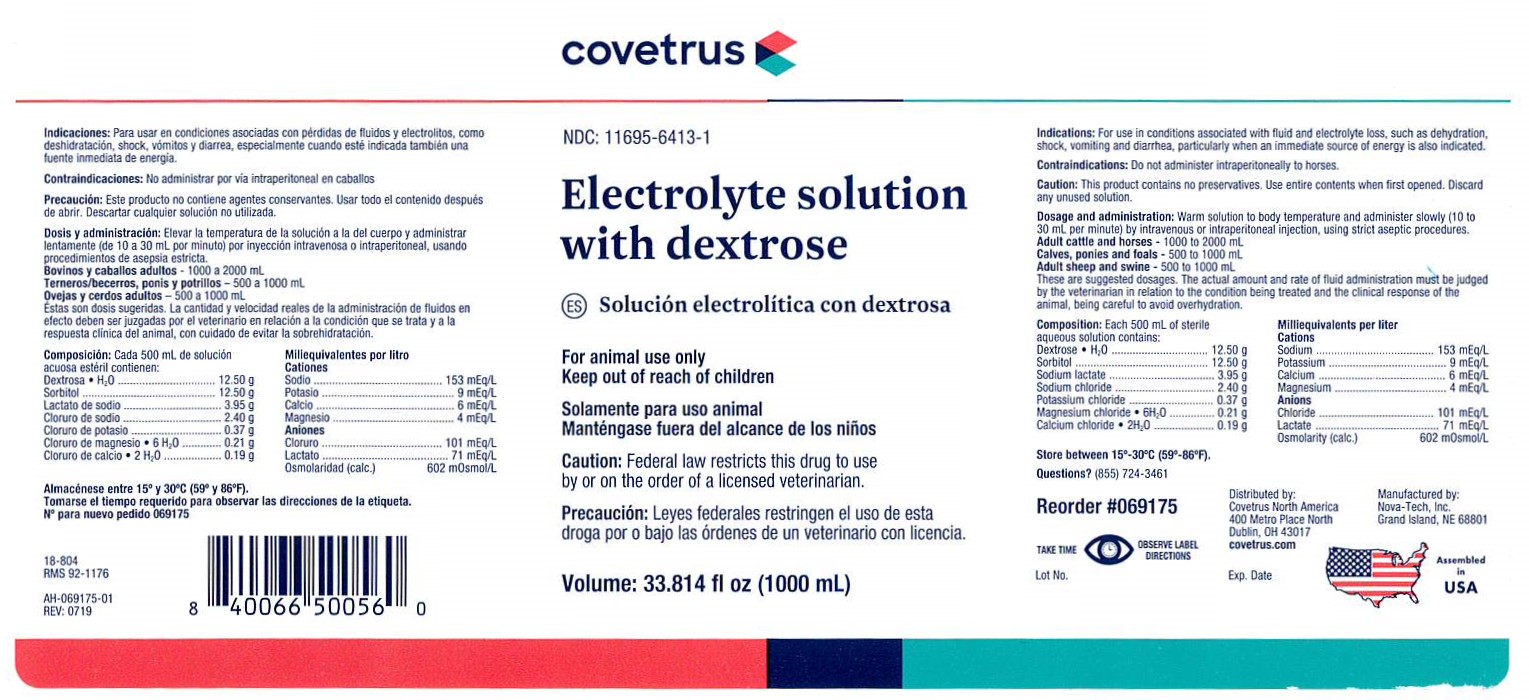 DRUG LABEL: Electrolyte solution with dextrose
NDC: 11695-6413 | Form: INJECTION, SOLUTION
Manufacturer: Covetrus
Category: animal | Type: PRESCRIPTION ANIMAL DRUG LABEL
Date: 20240605

ACTIVE INGREDIENTS: Dextrose Monohydrate 12.50 g/500 mL; Sorbitol 12.50 1/500 mL; Sodium Lactate 3.95 1/500 mL; Sodium Chloride 2.40 1/500 mL; Potassium Chloride 0.37 1/500 mL; Magnesium Chloride 0.21 1/500 mL; Calcium Chloride 0.19 1/500 mL

Electrolyte solution with dextrose

INDICATIONS:

For use in conditions associated with
fluid and electrolyte loss, such as dehydration,
shock, vomiting and diarrhea, particularly when an
immediate source of energy is also indicated.

CONTRAINDICATIONS:

Do not administer intraperitoneally to horses.

CAUTION:

This product contains no preservatives.
Use entire contents when first opened. Discard any unused solution.

DOSAGE AND ADMINISTRATION:

Warm solution to
body temperature and administer slowly (10 to 30
mL per minute) by intravenous or intraperitoneal
injection, using strict aseptic procedures.

Adult Cattle and Horses - 1000 to 2000 mL
Calves, Ponies and Foals - 500 to 1000 mL

Adult Sheep and Swine - 500 to 1000 mL

These are suggested dosages. The actual amount
and rate of fluid administration must be judged by
the veterinarian in relation to the condition being
treated and the clinical response of the animal, being
careful to avoid overhydration.

PRECAUTIONS

TAKE TIME OBSERVE LABEL DIRECTIONS

INFORMATION FOR OWNERS/CAREGIVERS

Questions? (855) 724-3461

Reorder #069174

18-804

RMS 92-1175

AH-069174-01

Rev: 0719

Lot No.

Exp. Date

Manufactured by
Nova-Tech, Inc.
Grand Island, NE 68801

Distributed by:

Covetrus North America

400 Metro Place North

Dublin, OH 43017

Volume: 16.907 fl oz (500 mL)

Assembled in USA

VETERINARY INDICATIONS

FOR ANIMAL USE ONLY

KEEP OUT OF REACH OF CHILDREN

Caution:

Federal law restricts this drug to use by or on the order of a licensed veterinarian.

COMPOSITION:

Each 500 mL of sterile aqueous
solution contains:
Dextrose . H2O.........................12.50 g

Sorbitol...................................12.50 g

Sodium lactate.........................3.95 g

Sodium chloride........................2.40 g

Potassium chloride....................0.37 g

Magnesium chloride . 6H2O.........0.21 g

Calcium chloride . 2H2O..............0.19 g

Milliequivalents per liter

Cations

Sodium...................................153 mEq/L

Potassium..................................9 mEq/L

Calcium.....................................6 mEq/L

Magnesium................................4 mEq/L

Anions

Chloride..................................101 mEq/L

Lactate.....................................71 mEq/L

Osmolarity (calc.) 602 mOsmol/L

STORAGE AND HANDLING

Store between 15°-30°C (59°-86F).